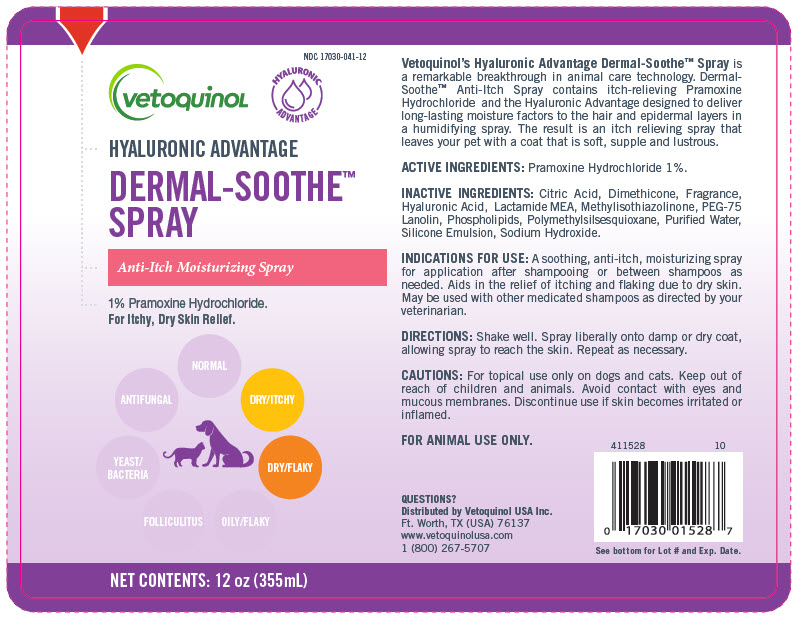 DRUG LABEL: Dermal-Soothe
NDC: 17030-041 | Form: SPRAY
Manufacturer: Vetoquinol USA, Inc.
Category: animal | Type: OTC ANIMAL DRUG LABEL
Date: 20241217

ACTIVE INGREDIENTS: Pramoxine Hydrochloride 10 mg/1 mL
INACTIVE INGREDIENTS: Citric Acid Monohydrate; DIMETHICONE; N-Lactoyl Ethanolamine; METHYLCHLOROISOTHIAZOLINONE; PEG-75 Lanolin; Water

Micro Pearls® Advantage
Dermal-Soothe™
Spray

Patented Continuous Moisture Release

INDICATIONS:

A soothing, anti-itch, moisturizing spray for application after shampooing or between shampoos as needed. Aids in the relief of itching and flaking due to dry skin. May be used with other medicated shampoos as directed by your veterinarian.

DESCRIPTION:

Micro Pearls® Advantage Dermal-Soothe™ Anti-Itch Spray is a remarkable breakthrough in animal care technology. Dermal-Soothe™ Anti-Itch Spray contains itch-relieving Pramoxine Hydrochloride and Novasome® microvesicles designed to deliver long-lasting moisture factors to the hair and epidermal layers in a humidifying spray containing Lactamide MEA. The result is an itch relieving spray that leaves your pet with a coat that is soft, supple and lustrous.

DIRECTIONS:

Shake well. Spray liberally onto damp or dry coat, allowing spray to reach the skin. Repeat as necessary.

ACTIVE INGREDIENTS:

Pramoxine Hydrochloride 1%

INACTIVE INGREDIENTS:

USP Purified Water, NM3, Lactamide MEA, Fragrance, Quaternium 15, Citric Acid.

CAUTIONS:

For topical use only on dogs and cats. Avoid contact with eyes and mucous membranes. Discontinue use if skin becomes irritated or inflamed.

WARNINGS

AVAILABLE ONLY THROUGH LICENSED VETERINARIANS. KEEP OUT OF REACH OF CHILDREN. FOR ANIMAL USE ONLY.

Novasome® is a registered trademark of Micro Pak, Inc.

QUESTIONS?

Manufactured for:
Vetoquinol USA, Inc.
Ft. Worth, TX (USA) 76137
1 (800) 267-5707
www.vetoquinolusa.com

411528
8

Lot

Exp. Date

PRINCIPAL DISPLAY PANEL - 355 mL Bottle Label

NDC 17030-041-12

vetoquinoL

HYALURONIC
ADVANTAGE

HYALURONIC ADVANTAGE

DERMAL-SOOTHE™
SPRAY

Anti-Itch Moisturizing Spray

1% Pramoxine Hydrochloride.
For Itchy, Dry Skin Relief.

NORMAL

ANTIFUNGAL

DRY/ITCHY

YEAST/
BACTERIA

DRY/FLAKY

FOLLICULITUS

OILY/FLAKY

NET CONTENTS: 12 oz (355mL)